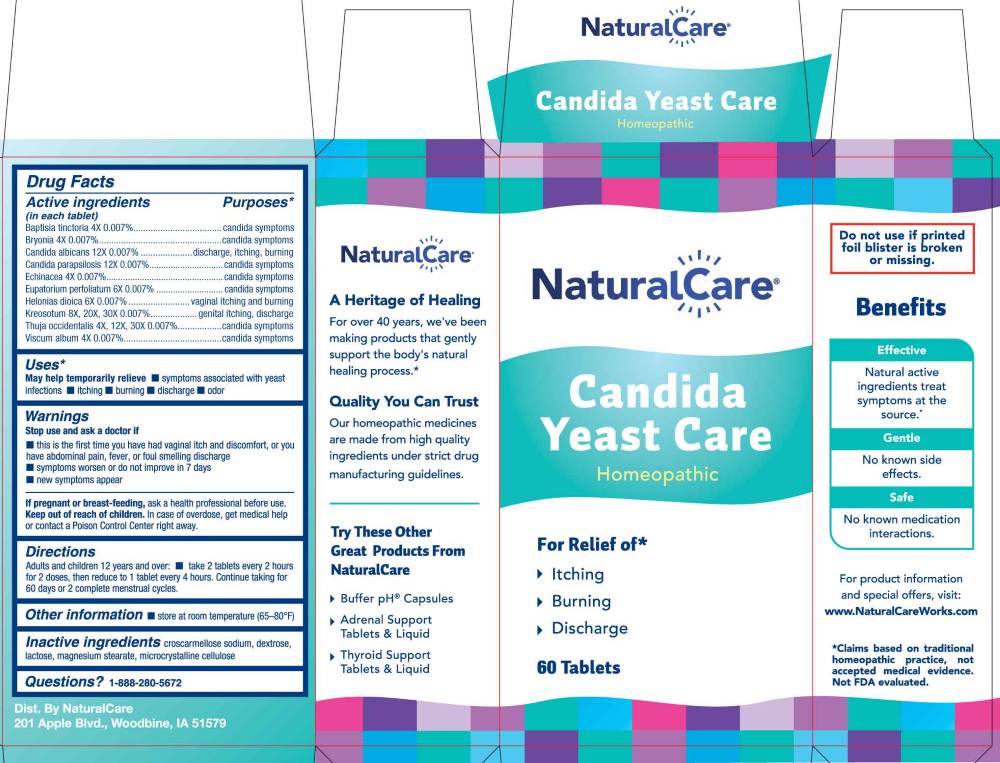 DRUG LABEL: Candida Yeast Care
NDC: 70163-0015 | Form: TABLET
Manufacturer: NaturalCare
Category: homeopathic | Type: HUMAN OTC DRUG LABEL
Date: 20260130

ACTIVE INGREDIENTS: BAPTISIA TINCTORIA WHOLE 4 [hp_X]/1 1; BRYONIA ALBA ROOT 4 [hp_X]/1 1; CANDIDA ALBICANS 12 [hp_X]/1 1; CANDIDA PARAPSILOSIS 12 [hp_X]/1 1; ECHINACEA ANGUSTIFOLIA WHOLE 4 [hp_X]/1 1; EUPATORIUM PERFOLIATUM FLOWERING TOP 6 [hp_X]/1 1; CHAMAELIRIUM LUTEUM ROOT 6 [hp_X]/1 1; WOOD CREOSOTE 8 [hp_X]/1 1; THUJA OCCIDENTALIS LEAFY TWIG 4 [hp_X]/1 1; VISCUM ALBUM FRUITING TOP 4 [hp_X]/1 1
INACTIVE INGREDIENTS: CROSCARMELLOSE SODIUM; DEXTROSE, UNSPECIFIED FORM; LACTOSE MONOHYDRATE; MAGNESIUM STEARATE; MICROCRYSTALLINE CELLULOSE

DRUG FACTS:

ACTIVE INGREDIENT:

(in each tablet) Baptisia Tinctoria 4X 0.007%, Bryonia 4X 0.007% , Candida Albicans 12X 0.007%, Candida Parapsilosis 12X 0.007%, Echinacea 4X 0.007%, Eupatorium Perfoliatum 6X 0.007%, Helonias Dioica 6X 0.007%, Kreosotum 8X, 20X, 30X, 0.007%, Thuja Occidentalis 4X, 12X, 30X, 0.007%, Viscum Album 4X 0.007%.

PURPOSE:

Baptisia Tinctoria – candida symptoms, Bryonia - candida symptoms , Candida Albicans – discharge, itching, burning, Candida Parapsilosis - candida symptoms, Echinacea - candida symptoms, Eupatorium Perfoliatum - candida symptoms, Helonias Dioica – vaginal itching and burning, Kreosotum – genital itching, discharge, Thuja Occidentalis candida symptoms, Viscum Album - candida symptoms*

*Claims based on traditional homeopathic practice, not accepted medical evidence. Not FDA evaluated.

USES:

May help temporarily relieve

• symptoms associated with yeast infection • itching • burning • discharge • odor*

*Claims based on traditional homeopathic practice, not accepted medical evidence. Not FDA evaluated.

WARNINGS:

Stop use and ask a doctor if

• this is the first time you have had vaginal itch and discomfort, or you have abdominal pain, fever, or foul smelling discharge.

•symptoms worsen or do not improve in 7 days

• new symptoms occur

If pregnant or breast-feeding, ask a health professional before use.

Keep out of reach of children. In case of overdose, get medical help or contact a Poison Control Center right away.

Do not use if printed foil blister is broken or missing.

• Store at room temperature (65-80ºF)

KEEP OUT OF REACH OF CHILDREN:

In case of overdose, get medical help or contact a Poison Control Center right away.

DIRECTIONS:

Adults and children 12 years and over:

• take 2 tablets every 2 hours for 2 doses, then reduce to 1 tablet every 4 hours. Continue taking for 60 days or 2 complete menstrual cycles.

INACTIVE INGREDIENTS:

croscarmellose sodium, dextrose, lactose, magnesium stearate, microcrystalline cellulose

QUESTIONS:

Dist. By NaturalCare

201 Apple Blvd.

Woodbine, IA 51579

www.NaturalCareWorks.com

1-888-280-5672

PACKAGE LABEL DISPLAY:

NaturalCare

Candida Yeast Care

Homeopathic

For Relief of*

Itching

Buring

Discharge

60 Tablets